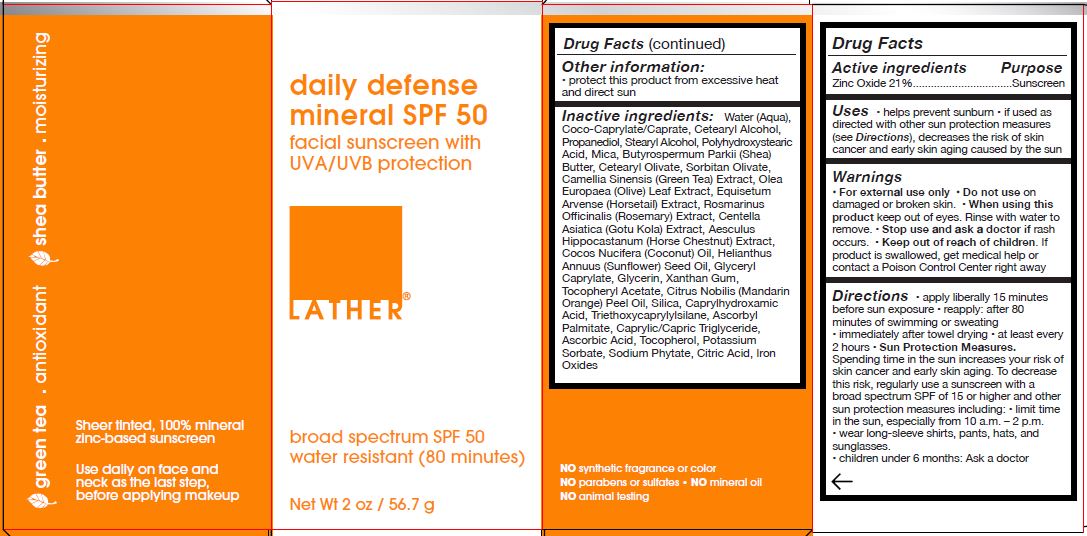 DRUG LABEL: LATHER- DAILY DEFENSE MINERAL SPF 50
NDC: 77394-202 | Form: CREAM
Manufacturer: Lather, Inc.
Category: otc | Type: HUMAN OTC DRUG LABEL
Date: 20251015

ACTIVE INGREDIENTS: ZINC OXIDE 21 g/100 g
INACTIVE INGREDIENTS: COCO-CAPRYLATE/CAPRATE; CETYL ALCOHOL; PROPANEDIOL; WATER; STEARYL ALCOHOL; POLYHYDROXYSTEARIC ACID (2300 MW); MICA; BUTYROSPERMUM PARKII (SHEA) BUTTER UNSAPONIFIABLES; CETEARYL OLIVATE; SORBITAN OLIVATE; CAMELLIA SINENSIS FLOWER; OLEA EUROPAEA (OLIVE) OIL UNSAPONIFIABLES; EQUISETUM ARVENSE WHOLE; ROSMARINUS OFFICINALIS FLOWER; CENTELLA ASIATICA; AESCULUS HIPPOCASTANUM FLOWER; COCOS NUCIFERA WHOLE; HELIANTHUS ANNUUS SEED WAX; GLYCERYL CAPRYLATE; GLYCERIN; XANTHAN GUM; .ALPHA.-TOCOPHEROL ACETATE; CITRUS NOBILIS; SILICON DIOXIDE; CAPRYLHYDROXAMIC ACID; TRIETHOXYCAPRYLYLSILANE; ASCORBYL PALMITATE; CAPRYLIC/CAPRIC/SUCCINIC TRIGLYCERIDE; ASCORBIC ACID; TOCOPHEROL; POTASSIUM SORBATE; PHYTATE SODIUM; CITRIC ACID ACETATE; BROWN IRON OXIDE

LATHER - DAILY DEFENSE MINERAL SPF 50 (77394-202)

ACTIVE INGREDIENTS

Zinc Oxide 21%

PURPOSE

Sunscreen

USES

- helps prevent sunburn
- if used as directed with other sun protection measures (see Directions), decreases the risk of skin cancer and early skin aging caused by the sun

WARNINGS

- For external use only
- Do not use on damaged or broken skin
- When using this product keep out of eyes. Rinse with water to remove.
- Stop use and ask a doctor if rash occurs

Keep out of reach of children. If product is swallowed, get medical help or contact a Poison Control Center right away.

DIRECTIONS

- Apply liberally 15 minutes before sun exposure
- reapply: after 80 minutes of swimming or sweating
- immediately after towel drying
- at least every 2 hours
- Sun Protection Measures. Spending time in the sun increases your risk of skin cancer and early skin aging. To decrease this risk, regularly use a sunscreen with a Broad Spectrum SPF of 15 or higher and other sun protection measures including:
- limit time in the sun, especially from 10 a.m. - 2 p.m.
- wear long-sleeve shirts, pants, hats, and sunglasses
- children under 6 months of age: ask a doctor

OTHER INFORMATION

- Protect this product from excessive heat and direct sun

INACTIVE INGREDIENTS

Water (aqua), Coco-Caprylate/Caprate, Cetearyl Alcohol, Propanediol, Stearyl Alcohol, Polyhydroxystearic Acid, Mica, Butyrospermum Parkii (Shea) Butter, Cetearyl Olivate, Sorbitan Olivate, Camellia Sinensis (Green Tea) Extract, Olea Europaea (Olive) Leaf Extract, Equisetum Arvense (Horsetail) Extract, Rosmarinus Officinalis (rosemary) Extract, Centella Asiatica (Gotu Kola) Extract, Aesculus Hippocastanum (Horse Chestnut) Extract, Cocos Nucifera (Coconut) Oil, Helianthus Annuus (Sunflower) Seed Oil, Glyceryl Caprylate, Glycerin, Xanthan Gum, Tocopheryl Acetate, Citrus Nobilis (Mandarin Orange) Peel Oil, Silica, Caprylhydroxamic Acid, Triethoxycaprylylsilane, Ascorbyl Palmitate, Caprylic/Capric Triglyceride, Ascorbic Acid, Tocopherol, Potassium Sorbate, Sodium Phytate, Citric Acid, Iron Oxides